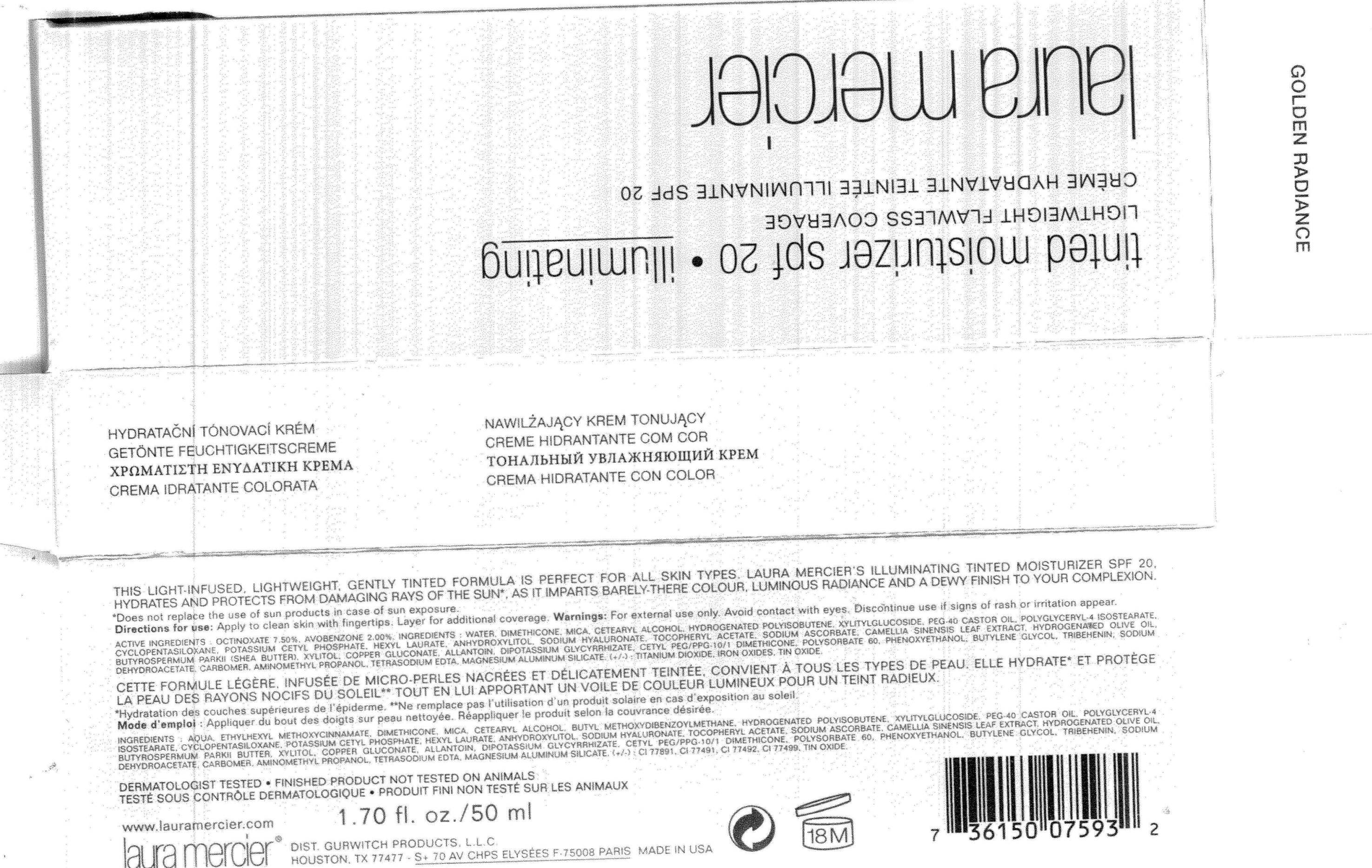 DRUG LABEL: Tinted Moisturizer SPF-20 Golden Radiance
NDC: 65342-1393 | Form: CREAM
Manufacturer: Gurwitch Products, L.L.C.
Category: otc | Type: HUMAN OTC DRUG LABEL
Date: 20110502

ACTIVE INGREDIENTS: Octinoxate 3 mL/40 mL; Avobenzone 0.8 mL/40 mL
INACTIVE INGREDIENTS: Water; Dimethicone; POLYGLYCERYL-4 ISOSTEARATE; CETOSTEARYL ALCOHOL; HEXYL LAURATE; .ALPHA.-TOCOPHEROL ACETATE, D-; SODIUM DEHYDROACETATE; HYALURONATE SODIUM; ALLANTOIN; SODIUM ASCORBATE; POLYSORBATE 60; PHENOXYETHANOL

ACTIVE INGREDIENT

Octinoxate (7.5%) , Avobenzone (2.0%)

WARNINGS

WARNINGS : FOR EXTERNAL USE ONLY.AVOID CONTACT WITH EYES. IF CONTACT OCCURS. RINSE THOROUGH WITH WATER.

Keep out of reach of children.

INDICATIONS AND USAGE

Direction for use : Apply to clean skin with fingertips. Layer for additional coverage.

INACTIVE INGREDIENT

Other Ingredients : Water , Dimethicone , Mica ,Cetearyl Alcohol , Hydrogenated Polyisobutene , Xyitilglucoside , PEG-40 Castor Oil ,Polyglyceryl-4 Isostearate , Cyclopentaxiloxane , Potassium Cetyl Phosphate , Hexyl Laurate ,Anhydroxylitol,Sodium Hyaluronate ,Tocopheryl Acetate ,Sodium Ascorbate , Camellia Sinensis Leaf Extract , Hydrogenated Olive Oil ,Butyrospermum Parkii(Shea Butter) , Xyritol , Copper Gluconate , Allantoin , Dipotassium Glycyrrhizate , Cetyl PEG/PPG-10/1 Dimethicone ,Polysorbate 60 , Phenoxyethanol ,Butylene Glycol ,Tribehenin ,Sodium Dehydroacetate ,Carbomer , Aminomethyl Propanol , Tetrasodium EDTA , Magenesium Aluminu Silicate,(+/-) :Titanium Dioxide , Iron Oxide, Tin Oxide